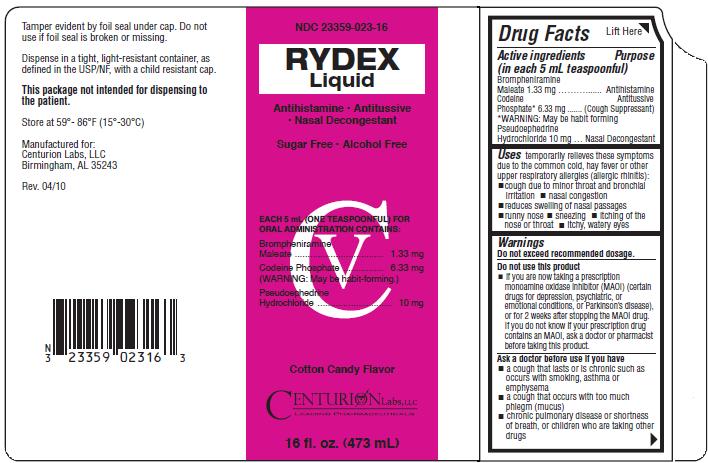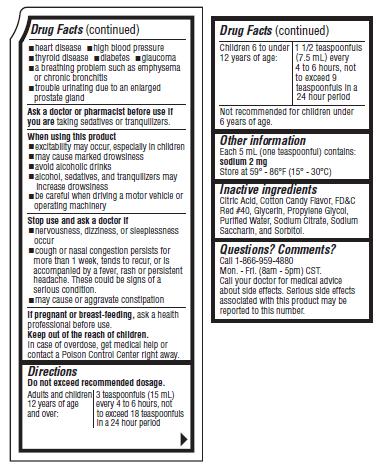 DRUG LABEL: Rydex
NDC: 23359-023 | Form: LIQUID
Manufacturer: Centurion Labs
Category: otc | Type: HUMAN OTC DRUG LABEL
Date: 20100611
DEA Schedule: CV

ACTIVE INGREDIENTS: Brompheniramine Maleate 1.33 mg/5 mL; Codeine Phosphate 6.33 mg/5 mL; Pseudoephedrine Hydrochloride 10 mg/5 mL

Rydex Liquid

Drug Facts

Active ingredients Purpose
(in each 5 mL teaspoonful)
Brompheniramine Maleate 1.33 mg..................................................Antihistamine
Codeine Phosphate*6.33 mg............................................................Antitussive
(Cough Suppressant)
*WARNING: May be habit forming
Pseudoephedrine Hydrochloride 10 mg.............................................Nasal Decongestant

Uses

temporarily relieves these symptoms due to the common cold, hay fever or other upper respiratory allergies (allergic rhinitis):

- cough due to minor throat and bronchial irritation
- nasal congestion
- reduces swelling of the nasal passages
- runny nose
- sneezing
- itching of the nose or throat
- itchy, water eyes

Warnings

Do not exceed recommended dosage.

Do not use this product

- if you are now taking a prescription monoamine oxidase inhibitor (MAOI) (certain drugs for depression, psychiatric, or emotional conditions, or Parkinson's disease), or for 2 weeks after stopping the MAOI drug. If you do not know if your prescription drug contains an MAOI, ask a doctor or pharmacist before taking this product.

Ask a doctor before use if you have

- a cough that lasts or is chronic such as occurs with smoking, asthma or emphysema
- a cough that occurs with too much phlegm (mucus)
- chronic pulmonary disease or shortness of breath, or children who are taking other drugs
- heart disease
- high blood pressure
- thyroid disease
- a breathing problem such as emphysema or chronic bronchitis
- trouble urinating due to an enlarged prostate gland

Ask a doctor or pharmacist before use if you are

taking sedatives or tranquilizers.

When using this product

- excitability may occur, especially in children
- may cause marked drowsiness
- avoid alcoholic drinks
- alcohol, sedatives, and tranquilizers may increase drowsiness
- be careful when driving a motor vehicle or operating machinery

Stop use and ask a doctor if

- nervousness, dizziness, or sleeplessness occur
- cough or nasal congestion persists for more than 1 week, tends to recur, or is accompanied by a fever, rash or persistent headache. These could be signs of a serious condition.
- may cause or aggravate constipation

If pregnant or breast-feeding,

ask a health professional before use.

Keep out of reach of children.

In case of overdose, get medical help or contact a Poison Control Center right away.

Directions

Do not exceed recommended dosage.

Adults and children 12 years of age and over: | 3 teaspoonfuls (15 mL) every 4 to 6 hours, not to exceed 18 teaspoonfuls in a 24 hour period.
Children 6 to under 12 years of age: | 1 1/2 teaspoonfuls (7.5 mL) every 4 to 6 hours, not to exceed 9 teaspoonfuls in a 24 hour period.
Not recommended for children under 6 years of age.

Other information

Each 5 mL (one teaspoonful) contains: sodium 2 mg
Store at 59° - 86°F (15° - 30°C)

Inactive ingredients

Citric Acid, Cotton Candy Flavor, FD and C Red #40, Glycerin, Propylene Glycol, Purified Water, Sodium Citrate, Sodium Saccharin, and Sorbitol.

Questions? Comments?

Call 1-866-959-4880
Mon. - Fri. (8am - 5pm) CST.
Call your doctor for medical advise about side effects. Serious side effects associated with this product may be reported to this number.

Product Packaging:

Packaging below represents the labeling currently used:
Principal display panel and side panel for 473 mL label:
NDC 23359-023-16
Rydex Liquid
Antihistamine/Antitussive/Nasal Decongestant
Sugar Free/Alcohol Free
Each 5mL (ONE TEASPOONFUL) FOR ORAL ADMINISTRATION CONTAINS:
Brompheniramine Maleate..............................1.33 mg
Codeine Phosphate........................................6.33 mg
(WARNING: May be habit-forming.)
Pseudoephedrine Hydrochloride.........................10 mg
CV
Cotton Candy Flavor
Centurion Labs, LLC
Leading Pharmaceuticals
16 fl. oz. (473 mL)
Tamper evident by foil seal under cap. Do not use if foil seal is broken or missing.
Dispense in a tight, light-resistant container, as defined in the USP/NF, with a child resistant cap.
This package not intended for dispensing to the patient.
Store at 59° - 86°F(15° - 30°C)
Manufactured for:
Centurion Labs, LLC
Birmingham, AL 35243
Rev. 04/10